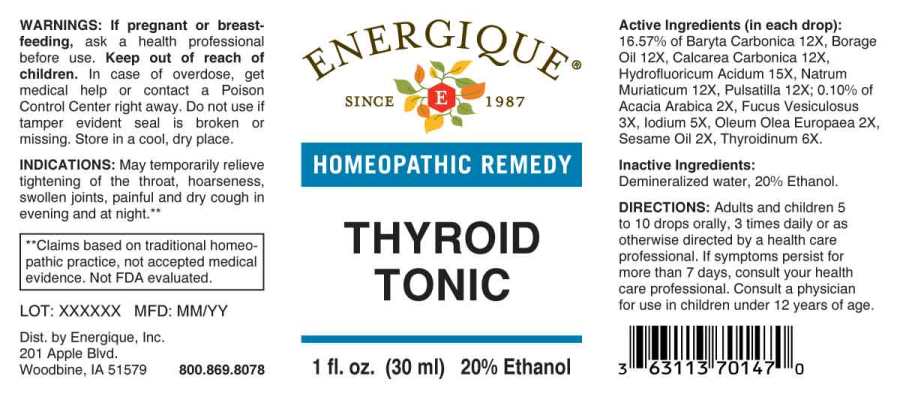 DRUG LABEL: Thyroid Tonic
NDC: 44911-0309 | Form: LIQUID
Manufacturer: Energique, Inc.
Category: homeopathic | Type: HUMAN OTC DRUG LABEL
Date: 20241031

ACTIVE INGREDIENTS: ACACIA 2 [hp_X]/1 mL; OLIVE OIL 2 [hp_X]/1 mL; SESAME OIL 2 [hp_X]/1 mL; FUCUS VESICULOSUS 3 [hp_X]/1 mL; IODINE 5 [hp_X]/1 mL; THYROID 6 [hp_X]/1 mL; BARIUM CARBONATE 12 [hp_X]/1 mL; BORAGE OIL 12 [hp_X]/1 mL; OYSTER SHELL CALCIUM CARBONATE, CRUDE 12 [hp_X]/1 mL; SODIUM CHLORIDE 12 [hp_X]/1 mL; PULSATILLA PRATENSIS WHOLE 12 [hp_X]/1 mL; HYDROFLUORIC ACID 15 [hp_X]/1 mL
INACTIVE INGREDIENTS: WATER; ALCOHOL

DRUG FACTS:

ACTIVE INGREDIENTS:

(in each drop): 16.57% of Baryta Carbonica 12X, Borage Oil 12X, Calcarea Carbonica 12X, Hydrofluoricum Acidum 12X, Natrum Muriaticum 12X, Pulsatilla (Pratensis) 12X; 0.10% of Acacia Arabica 2X, Fucus Vesiculosus 3X, Iodium 5X, Oleum Olea Europaea 2X, Sesame Oil 2X, Thyroidinum (Suis) 6X.

INDICATIONS:

May temporarily relieve tightening of the throat, hoarseness, swollen joints, painful and dry cough in evening and at night.**

**Claims based on traditional homeopathic practice, not accepted medical evidence. Not FDA evaluated.

WARNINGS:

If pregnant or breastfeeding, ask a health professional before use.

Keep out of reach of children. In case of overdose, get medical help or contact a Poison Control Center right away.

Do not use if tamper evident seal is broken or missing.

Store in a cool, dry place.

Keep out of reach of children. In case of overdose, get medical help or contact a Poison Control Center right away.

DIRECTIONS:

Adults and children 5 to 10 drops orally, 3 times daily or as otherwise directed by a health care professional. If symptoms persist for more than 7 days, consult your health care professional. Consult a physician for use in children under 12 years of age.

INDICATIONS:

May temporarily relieve tightening of the throat, hoarseness, swollen joints, painful and dry cough in evening and at night.**

**Claims based on traditional homeopathic practice, not accepted medical evidence. Not FDA evaluated.

INACTIVE INGREDIENTS:

Demineralized water, 20% Ethanol.

QUESTIONS:

Dist. by Energique, Inc.
201 Apple Blvd.
Woodbine, IA 51579 800.869.8078

PACKAGE LABEL DISPLAY:

ENERGIQUE

SINCE 1987

HOMEOPATHIC REMEDY

THYROID

TONIC

1fl. oz. (30 ml)